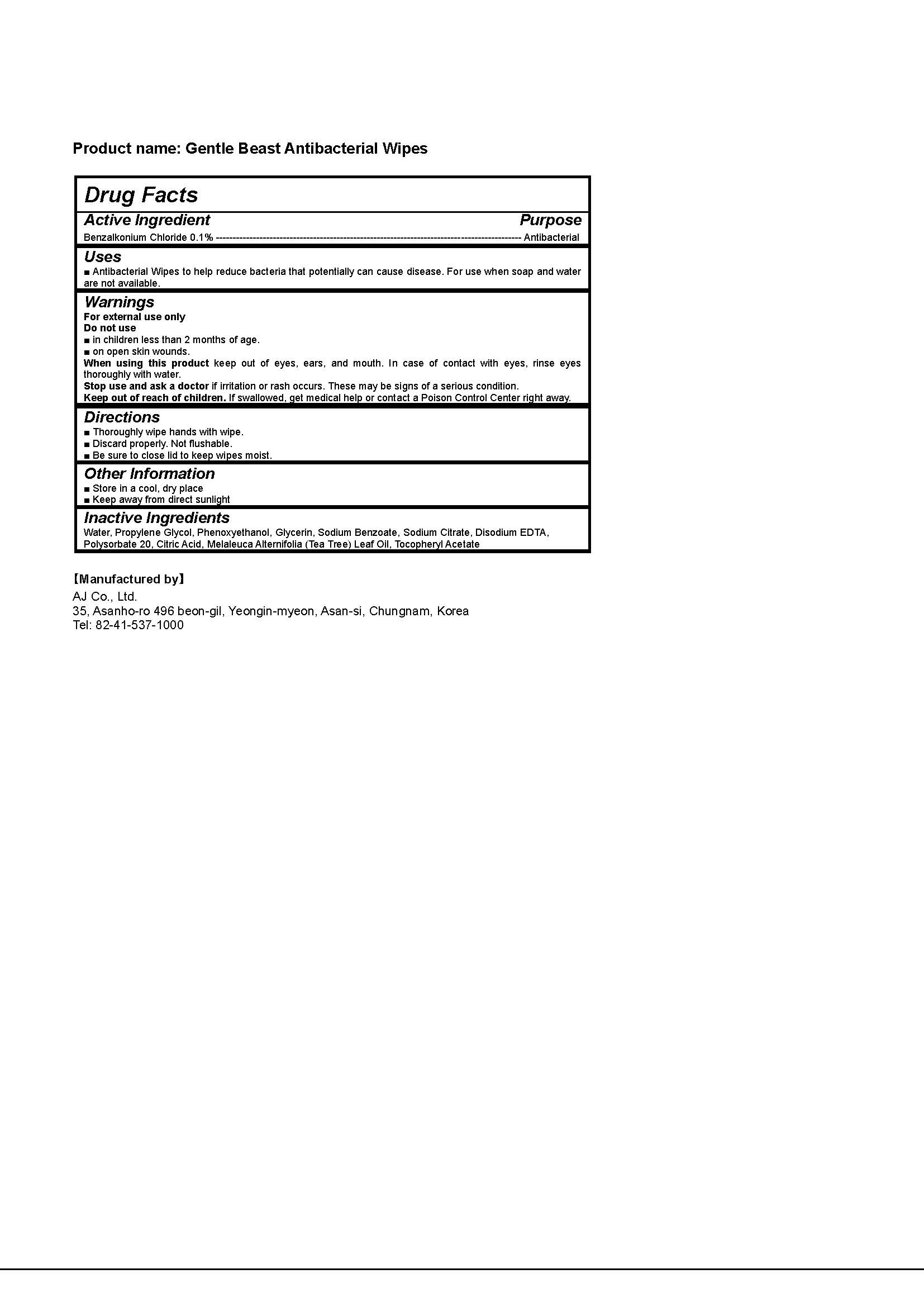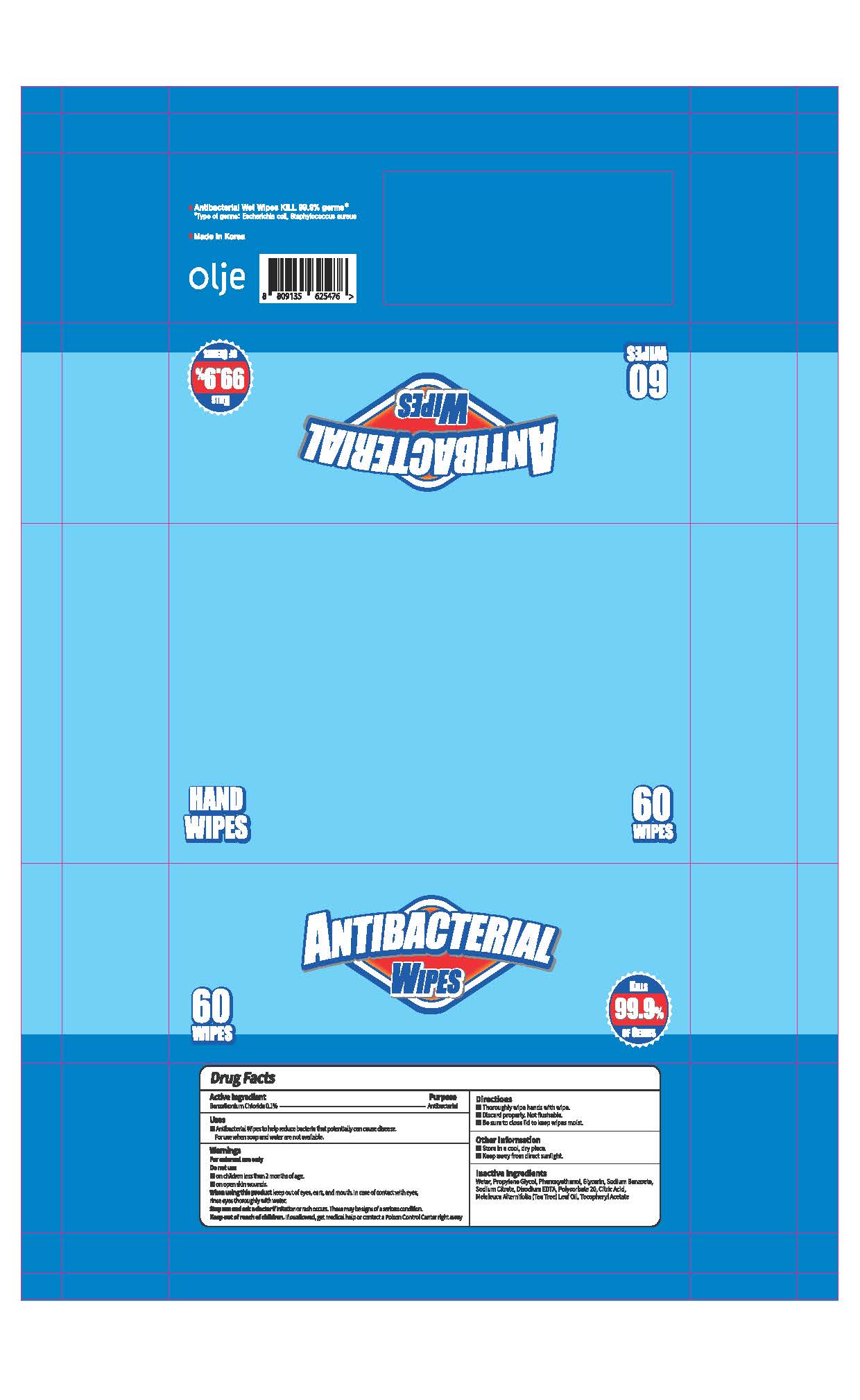 DRUG LABEL: Gentle Beast Antibacterial Wipes
NDC: 75356-0007 | Form: SWAB
Manufacturer: AJ Co., Ltd.
Category: otc | Type: HUMAN OTC DRUG LABEL
Date: 20210316

ACTIVE INGREDIENTS: BENZALKONIUM CHLORIDE 0.3 g/337 g
INACTIVE INGREDIENTS: .ALPHA.-TOCOPHEROL ACETATE; EDETATE DISODIUM ANHYDROUS; CITRIC ACID MONOHYDRATE; TEA TREE OIL; POLYSORBATE 20; PROPYLENE GLYCOL; PHENOXYETHANOL; SODIUM CITRATE; GLYCERIN; SODIUM BENZOATE; WATER

AJ Co., Ltd. - Gentle Beast Antibacterial Wipes

ACTIVE INGREDIENT

Benzalkonium Chloride

INACTIVE INGREDIENT

water, propylene glycol, phenoxyethanol, glycerin, sodium benzoate, sodium citrate, disodium edta, polysorbate 20, citric acid, melaleuca alternifolia (tea tree) leaf oil, tocopheryl acetate

PURPOSE

Antibacterial Wipes to help reduce bacteria that potentially can cause disease. For use when soap and water are not available.

keep out of reach of the children

INDICATIONS AND USAGE

Thoroughly wipe hands with wipe.

Discard properly. Not flushable.

Be sure to close lid to keep wipes moist.

WARNINGS

For external use only. Flammable. Keep away from heat or flame.

Do not use

- in children less than 2 months of age
- on open skin wounds

When using this product keep out of eyes, ears, and mouth. In case of contact with eyes, rinse thoroughly with water.

Stop use and ask a doctor if irritation or rash occurs. These may be signs of a serious condition.

Keep out of reach of children. If swallowed, get medical help or contact a Poison Control Center right away.

DOSAGE AND ADMINISTRATION

for external use only